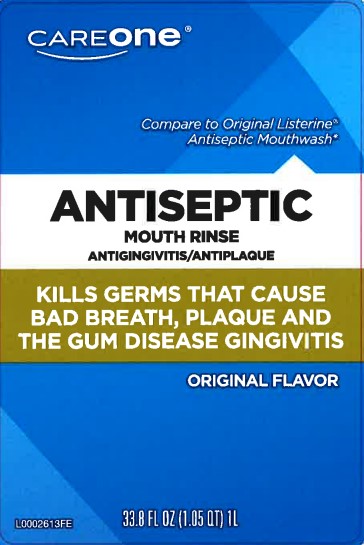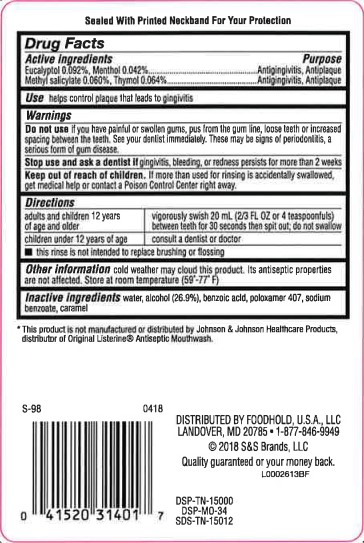 DRUG LABEL: Antiseptic Mouth Rinse
NDC: 72476-318 | Form: MOUTHWASH
Manufacturer: Retail Business Services, LLC
Category: otc | Type: HUMAN OTC DRUG LABEL
Date: 20260206

ACTIVE INGREDIENTS: EUCALYPTOL 0.92 mg/1 mL; MENTHOL 0.42 mg/1 mL; METHYL SALICYLATE 0.6 mg/1 mL; THYMOL 0.64 mg/1 mL
INACTIVE INGREDIENTS: WATER; ALCOHOL; BENZOIC ACID; POLOXAMER 407; SODIUM BENZOATE; CARAMEL

Care One 318.003/318AH-AI
Antiseptic Mouthrinse

TEP

Sealed With Printed Neckband For Your Protection

Active ingredients

Eucalyptol 0.092%

Menthol 0.042%

Methyl salicylate 0.060%

Thymol 0.064%

Purpose

Antigingivitis, Antiplaque

Use

helps control plaque that leads to gingvitis

Warnings

for this product

Do not use

if you have painful or swollen gums, pus from the gum line, loose teeth or increased spacing between the teeth. See your dentist immediately. These may be signs of periodontitis, a serious form of gum disease.

Stop use and ask a dentist if

gingivitis, bleeding, or redness persists for more than 2 weeks

Keep out of reach of children.

If more than used for rinsing is accidentally swallowed, get medical help or contact a Poison Control Center right away.

Directions

Adults and children 12 years of age and older - vigorously swish 20 ml (2/3 FL OZ or 4 teaspoonfruls) between teeth for 30 seconds then spit out; do not swallow

children under 12 years of age - consult a dentist or doctor

- this rinse is not intended to replace brushing or flossing

Other information

cold weather may cloud this product. Its antiseptic properties are not affected. Store at room temperature (59°-77°F).

Inactive ingredients

water, alcohol 26.9%, benzoic acid, poloxamer 407, sodium benzoate, caramel

Disclaimer

*This product is not manufactured or distributed by Johnson & Johnson Healthcare Products, distributor of Original ListerineAntiseptic Mouthwash.

Adverse Reaction

DISTRIBUTED BY FOODHOLD, U.S.A., LLC

LANDOVER, MD 20785

1-877-846-9949

© 2018 S&S Brands, LLC

Quality guaranteed or your money back.

DSP-TN-15000

DSP-MO-34

SDS-TN-15012

principal display panel

CAREONE®

Compare to Original Listerine®Antiseptic Mouthwash*

ANTISEPTIC

MOUTH RINSE

ANTIGINGIVITIS/ANTIPLAQUE

KILLS GERMS THAT CAUSE BAD BREATH, PLAQUE AND THE GUM DISEASE GINGIVITIS

ORIGINAL FLAVOR

33.8 FL OZ (1.05 QT) 1L